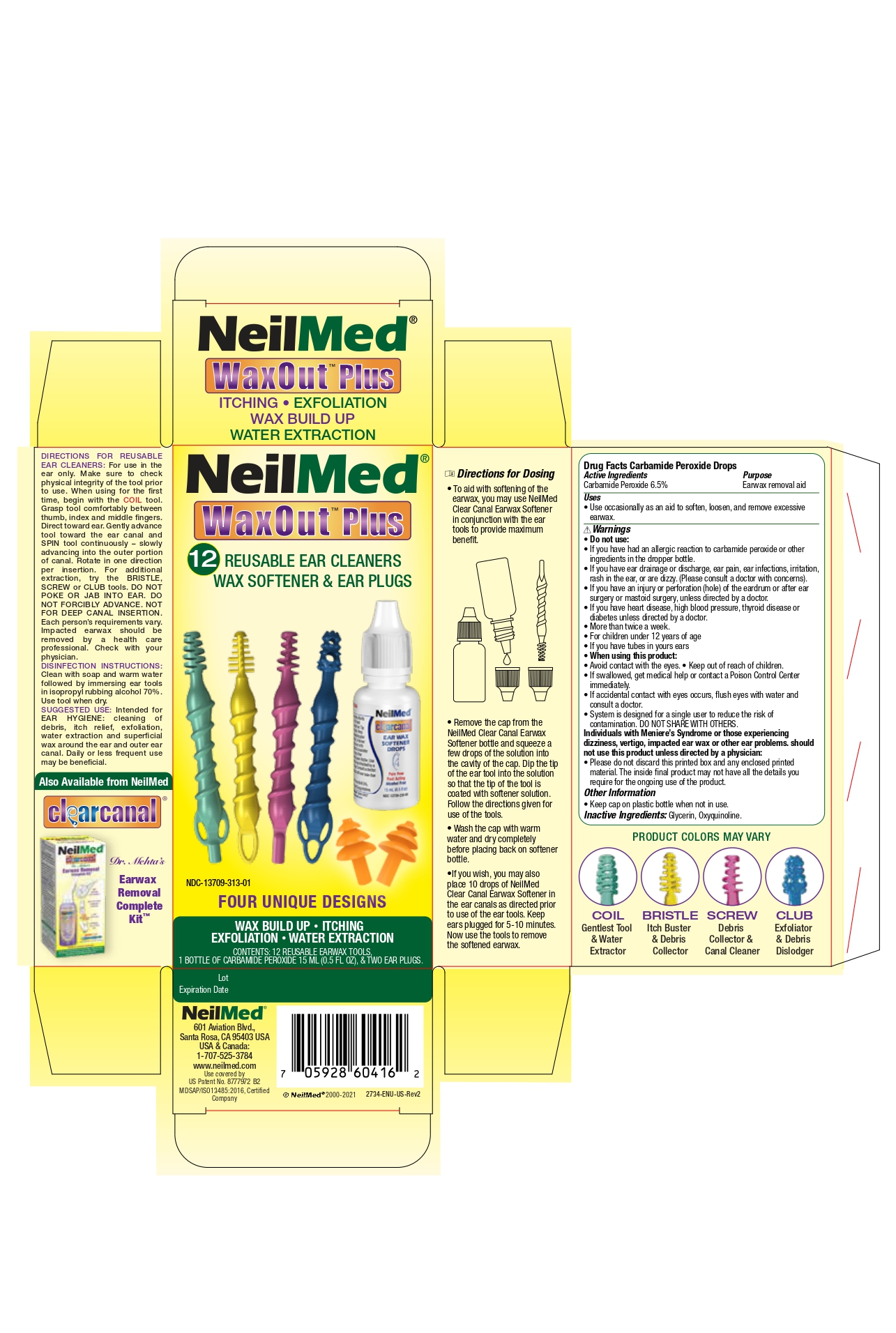 DRUG LABEL: Wax Out Plus
NDC: 13709-313 | Form: SOLUTION/ DROPS
Manufacturer: NEILMED PHARMACEUTICALS INC
Category: otc | Type: HUMAN OTC DRUG LABEL
Date: 20240111

ACTIVE INGREDIENTS: CARBAMIDE PEROXIDE 65 mg/1 mL
INACTIVE INGREDIENTS: OXYQUINOLINE; GLYCERIN

Waxout Plus

Drug Facts Carbamide Peroxide drops Active Ingredients

Carbamide Peroxide 6.5%

Purpose

Earwax Removal Aid

Uses

Use occasionally as an aid to soften, loosen , and remove excessive earwax.

Warnings

Do not use:

- If you have had an allergic reactionto carbamide peroxide or other ingredients in teh dropper bottle.
- If you have ear drainage or discharge, ear pain, ear infections, irritation, rash in the ear, or are dizzy. (Please consult a doctor with concerns).
- If you have an injury or perforation (hole) of the eardrum or after ear surgery or mastoid surgery, unless directed by a doctor.
- More than a twice a week.
- For children under 12 years of age.
- If you have tubes in your ears.

When using this product:

- Avoid contact with eyes
- Keep out of reach of children
- If swallowed, get medical help or contact a poison control center immediately.
- If accidental contact with eyes occurs, flush eyes with water and consult a doctor.
- System is designed for a single user to reduce the risk of contamination. DO NOT SHARE WITH OTHERS
- Individuals with Meniere's Syndrome or those experiencing dizziness, vertigo, impacted earwax or other ear problems should not use this product unless directed by a physician.
- Please do not discard this printed box and any enclosed printed material. The inside final product may not have all the details you require for the ongoing use of the product.

Other Information

- Keep cap on plastic bottle when not in use.

Inactive Ingredients

Glycerin, Oxyquinoline

Directions for ReUsable Ear Cleaners

For use in the ear only. Make sure to check physical integrity of the tool prior to use. When usingfor teh first time, begin with the COIL tool. Grasp tool comfortably between thumb, index and middle fingers. Direct toward ear. Gently advance tool toward the earcanal and SPIN tool continuously - slowly advancing into the outer portion of canal. Rotate in one direction per insertion. For additional extraction, try the BRISTLE, SCREW or CLUB tools. DO NOT POKE OR JAB INTO EAR. DO NOT FORCIBLY ADVANCE. NOT FOR DEEP CANAL INSERTION. Each person's requirements vary. Impacted earwax should be removed by a health care professional. Check with your physician.

DISINFECTIONS INSTRUCTIONS:

Clean with soap and warm water followed by immersing eartools in isopropyl rubbing alcohol 70%. Use tool when dry.

SUGGESTED USE:

Intended for EAR HYGIENE: Cleaning of debris, itch relief, exfoliation, water extraction and superficial wax around the ear and outer ear canal. Daily or less frequent use may be beneficial.

Directions for Dosing

- To aid with the softening of teh earwax, you may use NeilMed Clear Canal Earwax Softener in conjunction with the eartools to provide maiximum benefit.
- Remove the cap from the NeilMed Clear Canal EarWax Softener bottle and squuze a few drops of the solution into the cavity of the cap. Dip the tip of the ear tool into the solution so that the tip of the tool is coated with softener solution. Follow the directions given for use of the tools.
- Wash the cap with warm water and dry completely before placing back on softener bottle
- If you wish, you may also place 10 drops of NeilMed Claer Canal Earwax Softener in teh earcanals as directed prior to use of the eartools. Keep ear plugged for 5-10 minutes. Now use the tools to remove the softened earwax.

when Using this product

Keep out of reach of Children

Warnings :

Do not use:

If you have had an allergic reactionto carbamide peroxide or other ingredients in teh dropper bottle.
If you have ear drainage or discharge, ear pain, ear infections, irritation, rash in the ear, or are dizzy. (Please consult a doctor with concerns).
If you have an injury or perforation (hole) of the eardrum or after ear surgery or mastoid surgery, unless directed by a doctor.
More than a twice a week.
For children under 12 years of age.
If you have tubes in your ears.